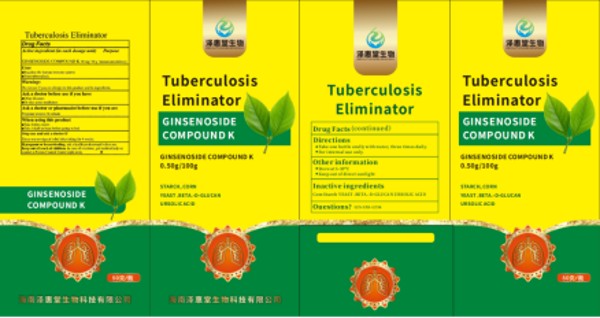 DRUG LABEL: TUBERCULOSIS ELIMINATOR
NDC: 84428-105 | Form: GRANULE
Manufacturer: Hainan Zehuitang Biotechnology Co., LTD
Category: homeopathic | Type: HUMAN OTC DRUG LABEL
Date: 20250526

ACTIVE INGREDIENTS: GINSENOSIDE COMPOUND K 50 mg/10 g
INACTIVE INGREDIENTS: URSOLIC ACID; YEAST .BETA.-D-GLUCAN; STARCH, CORN

84428-105-001

Active ingredient: Ginsenoside Compound K 50 mg/ 10 g

Purpose: Regulate the human immune system; Treat tuberculosis

Warnings:

Do not use if you are allergic to this product and its ingredients

Ask a doctor before use if you have

Other diseases;

Or take some medicines

Ask a doctor or pharmacist before use if you are Pregnant women Or infants

When using this product:

Take before meals,

Take it half an hour before going to bed

Stop use and ask a doctor if There was no sign of relief after taking for 4 weeks.

PREGNANCY OR BREAST FEEDING

If pregnant or breast-feeding, ask a health professional before use.

Keep out of reach of children. In case of overdose, get medical help or contact a Poison Control Center right away.

Directions:

Take one bottle orally with water, three times daily.

For internal use only.

INACTIVE INGREDIENT

Inactive ingredients: CORN STAREH, YEAST. BETA. -D-GLUCAN, URSOLIC ACID

Questions? 123-555-1234

Other information:

Store at 5-30℃,

Keep out of direct sunlight

INDICATIONS AND USAGE

Use: Regulate the human immune system; Treat tuberculosis

When using this productTake before mealsTake it half an hour before going to bed